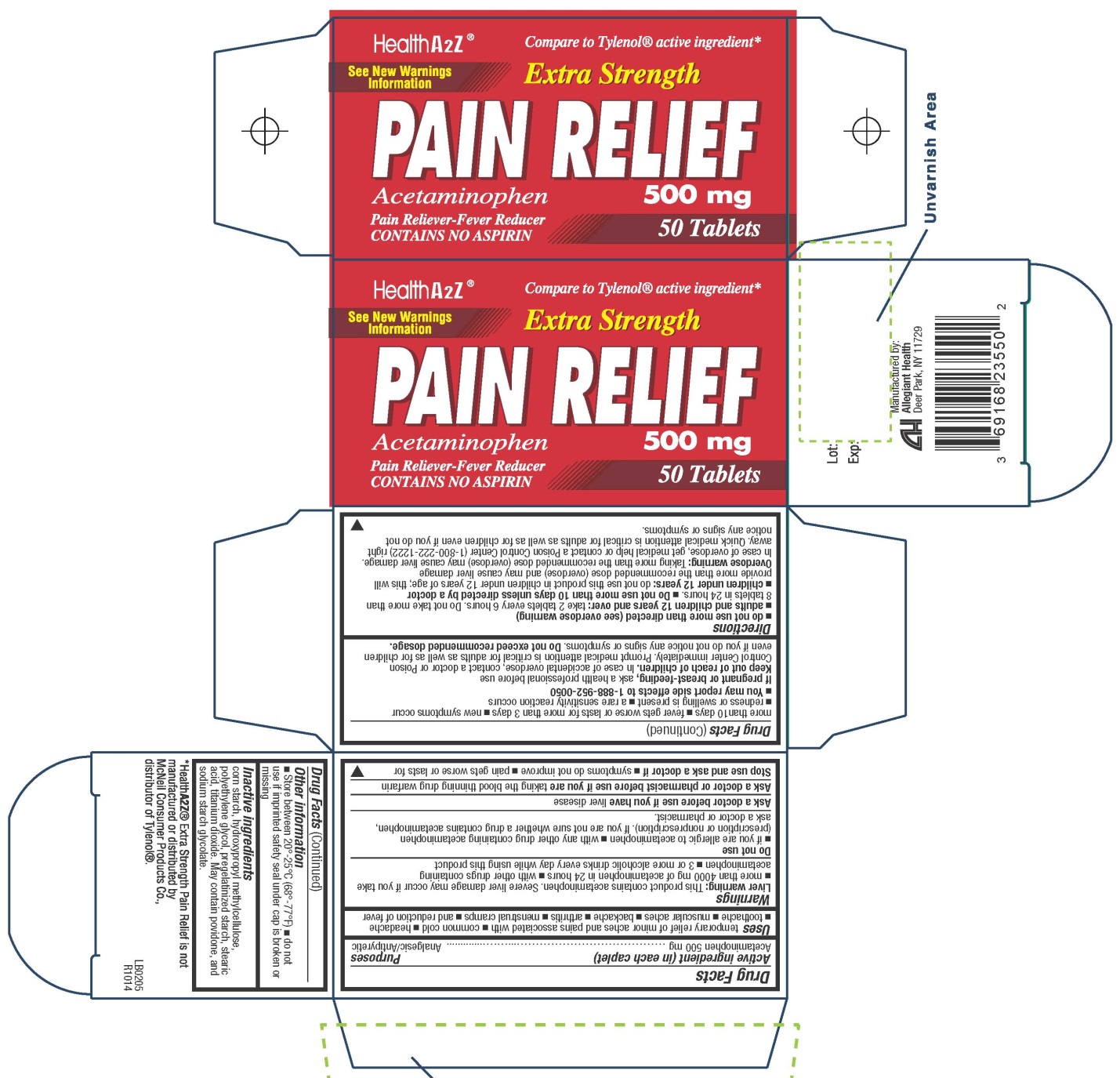 DRUG LABEL: Pain Relief
NDC: 69168-235 | Form: TABLET
Manufacturer: Allegiant Health
Category: otc | Type: HUMAN OTC DRUG LABEL
Date: 20141217

ACTIVE INGREDIENTS: ACETAMINOPHEN 500 mg/1 1
INACTIVE INGREDIENTS: STARCH, CORN; HYPROMELLOSES; POLYETHYLENE GLYCOLS; STEARIC ACID; TITANIUM DIOXIDE

Drug Facts

Active ingredient

Acetaminophen 500 mg

Purpose

Analgesic/Antipyretic

Uses

temporary relief of minor aches and pains associated with common cold headache toothache
muscular aches backache arthritis menstrual cramps and reduction of fever

Warnings

Liver warning: This product contains acetaminophen. Severe liver damage may occur if you takemore than 4000 mg of acetaminophen in 24 hours with other drugs containing acetaminophen 3 or more alcoholic drinks every day while using this product

Do not use

with any other drug containing acetaminophen (prescription or nonprescription). If you are not sure whether a drug contains acetaminophen, ask a doctor or pharmacist

Ask a doctor before use if you have

liver disease

Ask a doctor or pharmacist before use if you

are taking the blood thinning drug warfarin

Stop use and ask a doctor if

symptoms do not improve pain gets worse or lasts for more than 10 days ■ fever gets worse or lasts for more than 3 days new symptoms occur redness or swelling is present ■ a rare
sensitivity reaction occurs You may report side effects to 1-888-952-0050

If pregnant or breast-feeding

ask a health professional before use

Keep Out of Reach of Children

In case of accidental overdose, contact a doctor or Poison Control Center immediately. Prompt medical attention is critical for adults as well as for children even if you do not notice any signs or symptoms.
Do not exceed recommended dosage.

Directions

Adults and children 12 years of age and older: Take 2 tablets (1,000 mg) every 6 hours while symptoms last. Do not take more than 6 tablets (3,000 mg) in 24 hours, unless directed by a doctor.

Children under 12 years of age: Do not use this extra strength product. This will provide more than the recommended dose (overdose) and could cause serious health problems.

Inactive Ingredients

corn starch, hydroxypropyl methylcellulose, polyethylene glycol, pregelatinized starch, stearic acid, titanium dioxide. May contain povidone, and sodium starch glycolate.